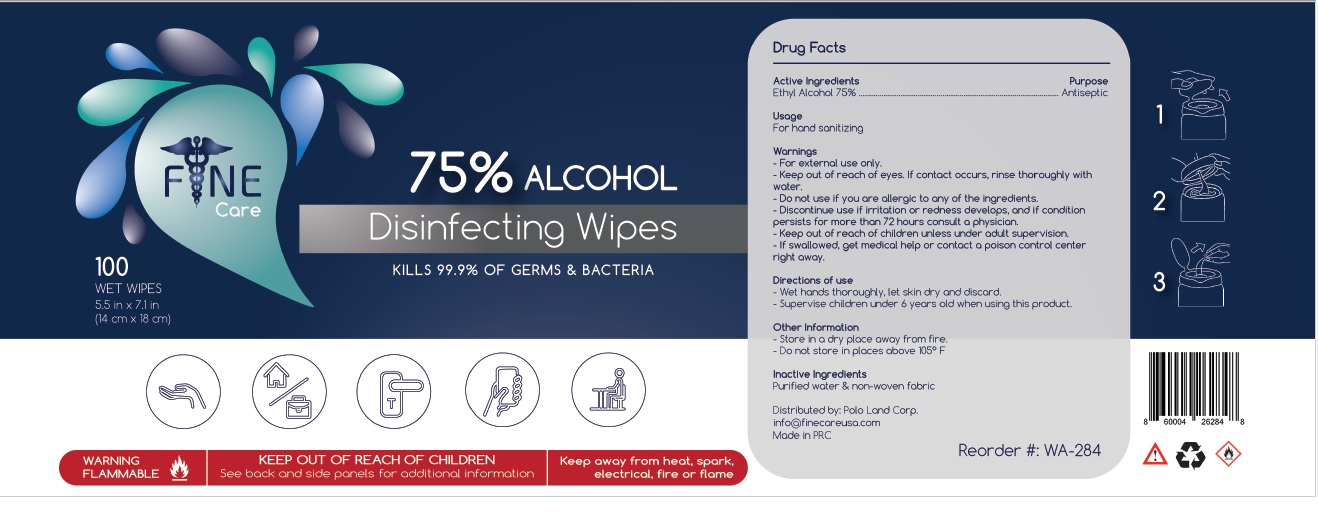 DRUG LABEL: FINECare 75% ALCOHOL Disinfecting Wipes
NDC: 78591-284 | Form: CLOTH
Manufacturer: Polo Land Corp
Category: otc | Type: HUMAN OTC DRUG LABEL
Date: 20200706

ACTIVE INGREDIENTS: ALCOHOL 75 mL/100 mL
INACTIVE INGREDIENTS: WATER

FINECare 75% ALCOHOL Disinfecting Wipes

Active Ingredients

Ethyl Alcohol 75%

Purpose

Antiseptic

Usage

For hand sanitizing

Warnings

- For external use only.

- Keep out of reach of eyes. If contact occurs, rinse thoroughly with water.

- Do not use if you are allergic to any of the ingredients.

- Discontinue use if irritation or redness develops, and if condition persists for more than 72 hours consult a physician.

- Keep out of reach of children unless under adult supervision.

- If swallowed, get medical help or contact a poison control center right away.

Directions of use

- Wet hands, surface or objects thoroughly with product and allow to dry without the use of water.
- Supervise children under 6 years old when using this product.

Other information

- Store in a dry place away from fire.
- Do not store in places above 105°F

Inactive Ingredients

Purified water & non-woven fabric

Distributed by: Polo Land Corp.
info@finecareusa.com
Made in PRC